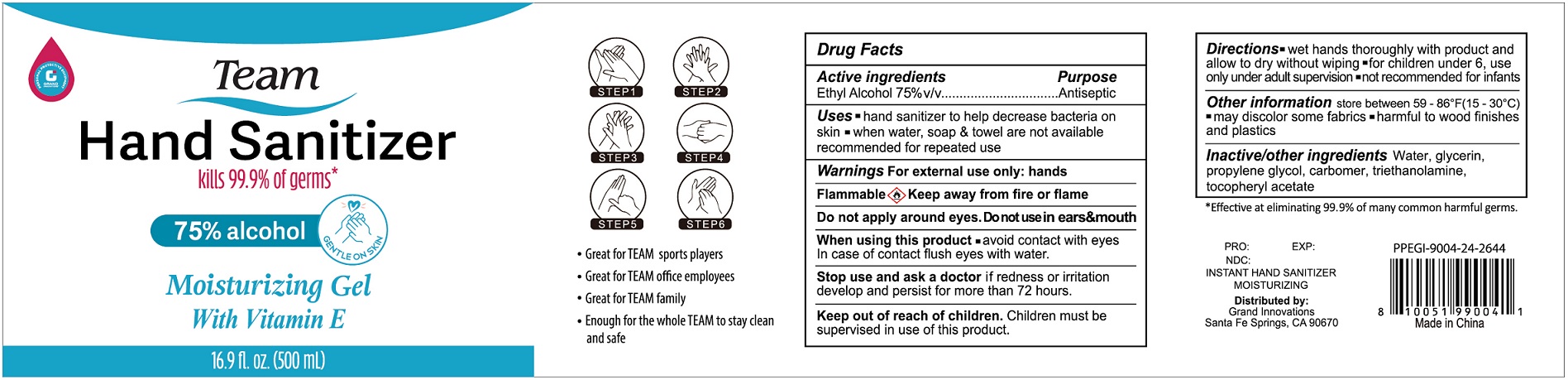 DRUG LABEL: Team Hand Sanitizer 75% alcohol Moisturizing Gel with Vitamin E
NDC: 54708-101 | Form: GEL
Manufacturer: Venus Skin & Hair Laboratory Ltd.
Category: otc | Type: HUMAN OTC DRUG LABEL
Date: 20200704

ACTIVE INGREDIENTS: ALCOHOL 375 mL/500 mL
INACTIVE INGREDIENTS: GLYCERIN; CARBOMER INTERPOLYMER TYPE A (ALLYL SUCROSE CROSSLINKED); WATER; PROPYLENE GLYCOL; TROLAMINE

Team, Hand Sanitizer, 75% Ethyl Alcohol, Liquid, 500mL, Bottle-Pump

Active Ingredient(s)

Ethyl Alcohol 75% v/v. Purpose: Antiseptic

Purpose

Antiseptic.

Uses

- hand sanitizer to help decrease bacteria on skin
- when water, soap & towel are not available

recommended for repeated use

Warnings

For external use only: hands.

Flammable. Keep away from fire or flame.

Do not use

Do not apply around eyes.

Do not use in ears & mouth.

When using this product, avoid contact with eyes.

In case of contact, flush eyes with water.

Stop use and ask a doctor if redness or irritation develop and persist for more than 72 hours.

Keep out of reach of children.

Children must be supervised in use of this product.

Directions

- wet hands thoroughly with product and allow to dry without wiping
- for children under 6, use only under adult supervision
- not recommended for infants

Other information

- Store between 59 - 86℉ (15 - 30℃)
- may discolor some fabrics
- harmful to wood finishes and plastics

Inactive ingredients

Water, Glycerin, Propylene glycol, Carbomer, Triethanolamine.